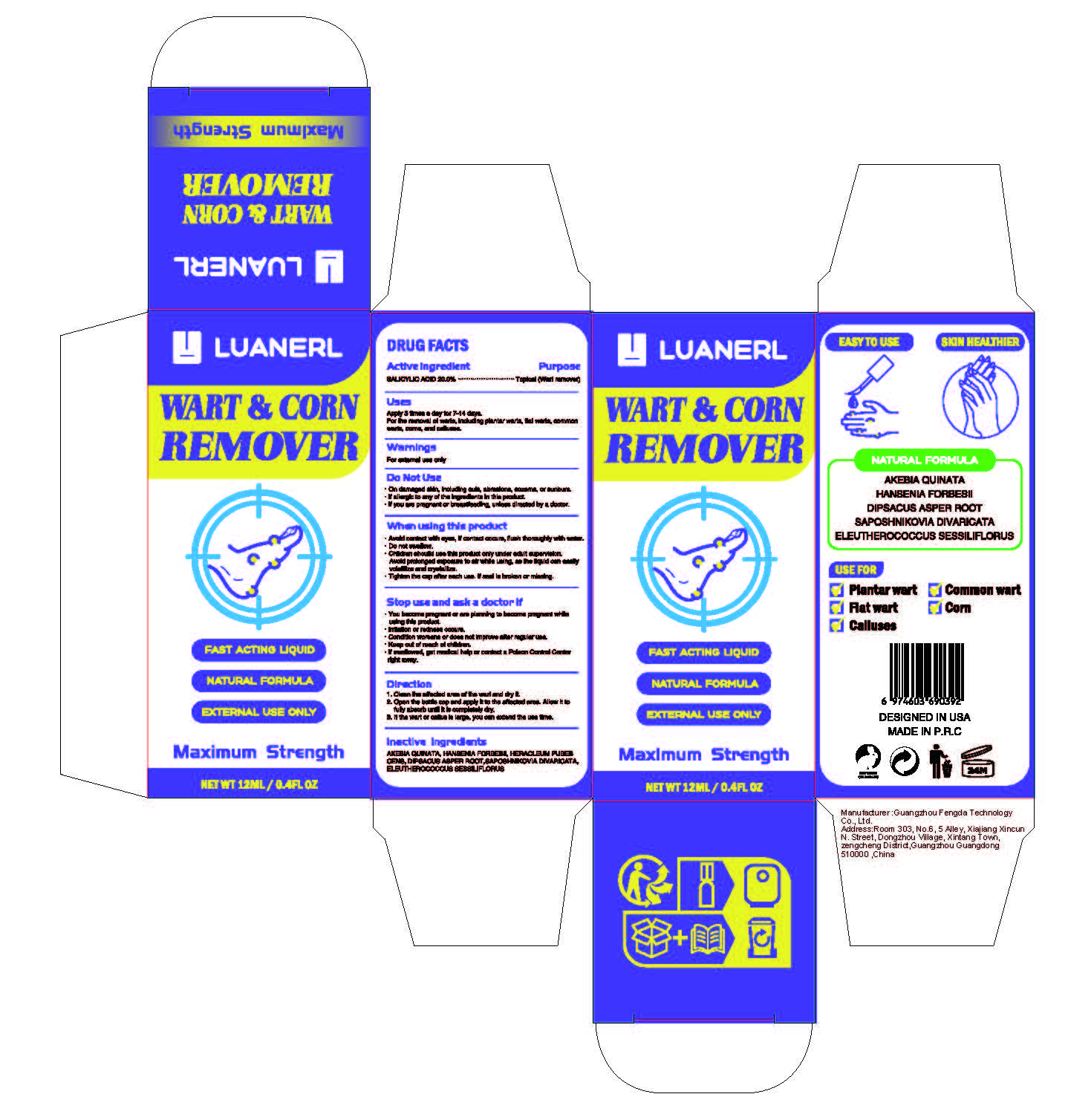 DRUG LABEL: wart  corn remover
NDC: 85595-001 | Form: LIQUID
Manufacturer: Guangzhou Fengda Technology Co., Ltd.
Category: otc | Type: HUMAN OTC DRUG LABEL
Date: 20250502

ACTIVE INGREDIENTS: SALICYLIC ACID 2.4 mg/12 mL
INACTIVE INGREDIENTS: HERACLEUM PUBESCENS WHOLE; DIMETHYL SULFOXIDE; ELEUTHEROCOCCUS SESSILIFLORUS WHOLE; AKEBIA QUINATA WHOLE; DIPSACUS ASPER ROOT; SAPOSHNIKOVIA DIVARICATA WHOLE; MENTHOL, (+)-; HANSENIA FORBESII WHOLE

ACTIVE INGREDIENT

SALICYLIC ACID 20.0%

PURPOSE

Plantar wart
Flat wart

Calluses

WARNINGS

For external use only

STOP USE

You become pregnant or are planning to become pregnant whileusing this product.
lrritation or redness occurs.Condition worsens or does not improve after regular use.Keep out of reach of chlldren.If swallowed, get medical help or contact a Poison Control Centerright away.

DO NOT USE

On damaged skin, including cuts, abrasions, eczema, or sunbum.
If allergic to any of the ingredients in this product.
if you are pregnant or breastfeeding, unless directed by a doctor.

Keep out of reach of children.

INDICATIONS AND USAGE

1. Clean the affected area of the wart and dry it.2. Open the bottle cap and apply it to the affected area. Allow it tofuly absorb until it is completely dry.3. lf the wart or callus is large, you can extend the use time.

DOSAGE AND ADMINISTRATION

Apply 3 times a day for 7-14 days.For the removal of warts, incuding plantar warts, fat warts, commonwarts, corns, and caluses,

WHEN USING

Avoid contact with eyes, if contact occurs, flush thoroughly with water,Do not swallow.Children shouild use this product only under adult supervision.Avoid prolonged exposure to air while using, as the liquid can easilyvolatilize and crystalize.Tighten the cap after each use. lf seal is broken or missing.